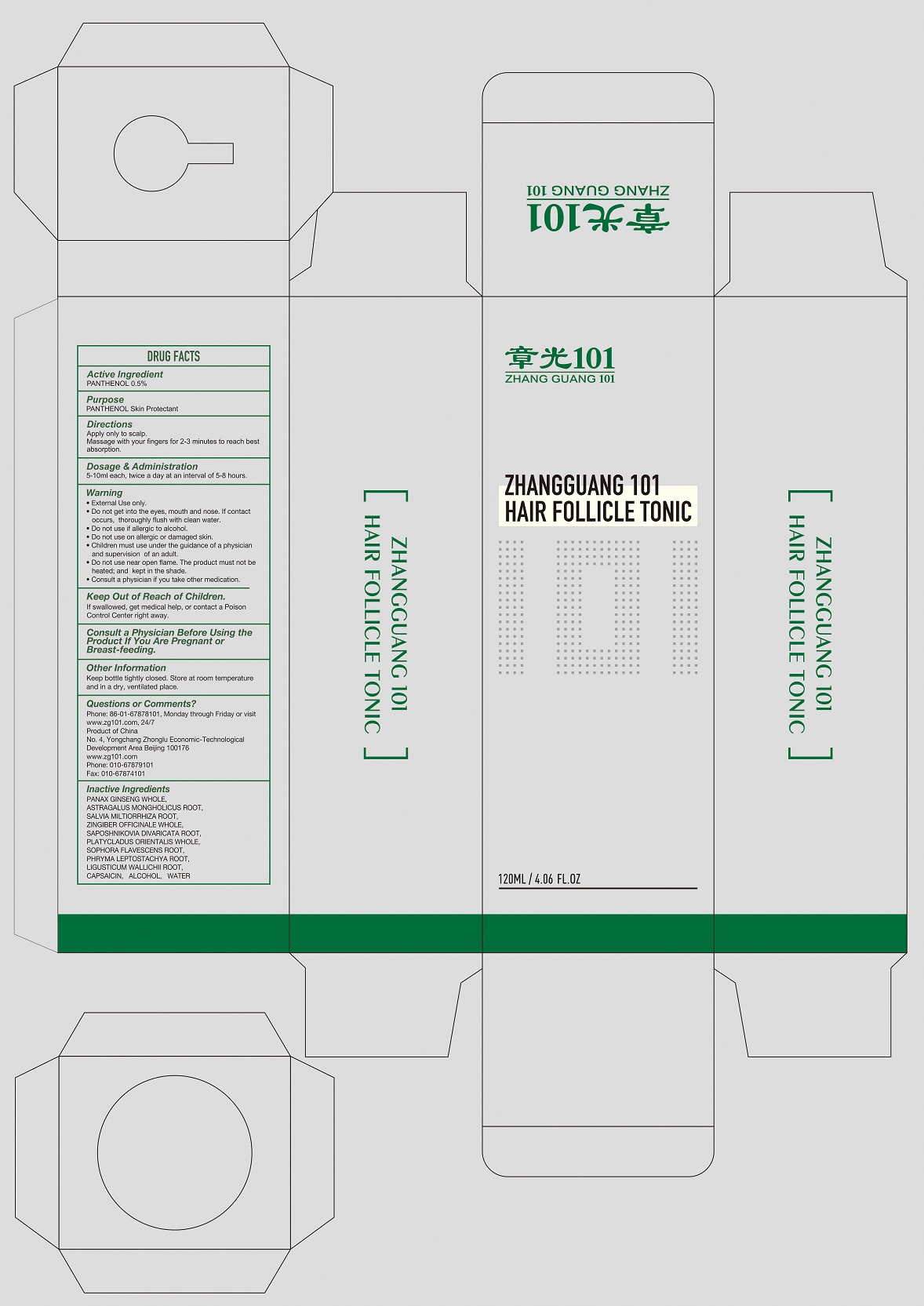 DRUG LABEL: ZHANGGUANG 101 HAIR FOLLICLE TONIC
NDC: 71675-005 | Form: LIQUID
Manufacturer: BEIJING ZHANGGUANG 101 SCIENCE & TECHNOLOGY CO, LTD
Category: otc | Type: HUMAN OTC DRUG LABEL
Date: 20211223

ACTIVE INGREDIENTS: PANTHENOL 0.5 g/100 mL
INACTIVE INGREDIENTS: PANAX GINSENG WHOLE; ASTRAGALUS MONGHOLICUS ROOT; SALVIA MILTIORRHIZA ROOT; ZINGIBER OFFICINALE WHOLE; SAPOSHNIKOVIA DIVARICATA ROOT; PLATYCLADUS ORIENTALIS WHOLE; SOPHORA FLAVESCENS ROOT; PHRYMA LEPTOSTACHYA ROOT; LIGUSTICUM WALLICHII ROOT; CAPSAICIN; ALCOHOL; WATER

BEIJING ZHANGGUANG 101 SCIENCE & TECHNOLOGY CO, LTD

Active Ingredients

PANTHENOL 0.5%

Purpose

PANTHENOL Skin Protectant

Directions

Apply only to scalp.
Massage with your fingers for 2-3 minutes to reach best absorption.

Dosage & Administration

5-10ml each, twice a day at an interval of 5-8 hours.

Warning

• External Use only.
• Do not get into the eyes, mouth and nose. If contact occurs, thoroughly flush with clean water.
• Do not use if allergic to alcohol.
• Do not use on allergic or damaged skin.
• Children must use under the guidance of a physician and supervision of an adult.
• Do not use near open flame. The product must not be heated; and kept in the shade.
• Consult a physician if you take other medication.

Keep Out of Reach of Children.

If swallowed, get medical help, or contact a Poison Control Center right away.

Other Information

Keep bottle tightly closed. Store at room temperature and in a dry, ventilated place.

Questions or Comments?

Phone: 86-01-67878101, Monday through Friday or visit www.zg101.com, 24/7
Product of China
No. 4, Yongchang Zhonglu Economic-Technological Development Area Beijing 100176
www.zg101.com
Phone: 010-67879101
Fax: 010-67874101

Inactive Ingredients

PANAX GINSENG WHOLE, ASTRAGALUS MONGHOLICUS ROOT, SALVIA MILTIORRHIZA ROOT, ZINGIBER OFFICINALE WHOLE, SAPOSHNIKOVIA DIVARICATA ROOT, PLATYCLADUS ORIENTALIS WHOLE, SOPHORA FLAVESCENS ROOT, PHRYMA LEPTOSTACHYA ROOT, LIGUSTICUM WALLICHII ROOT, CAPSAICIN, ALCOHOL, WATER